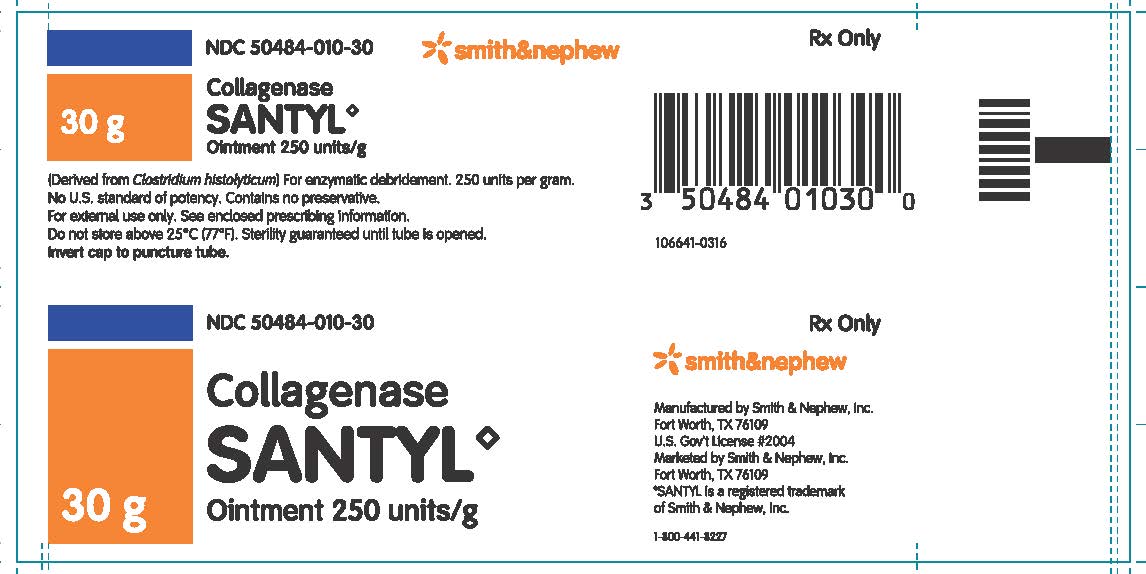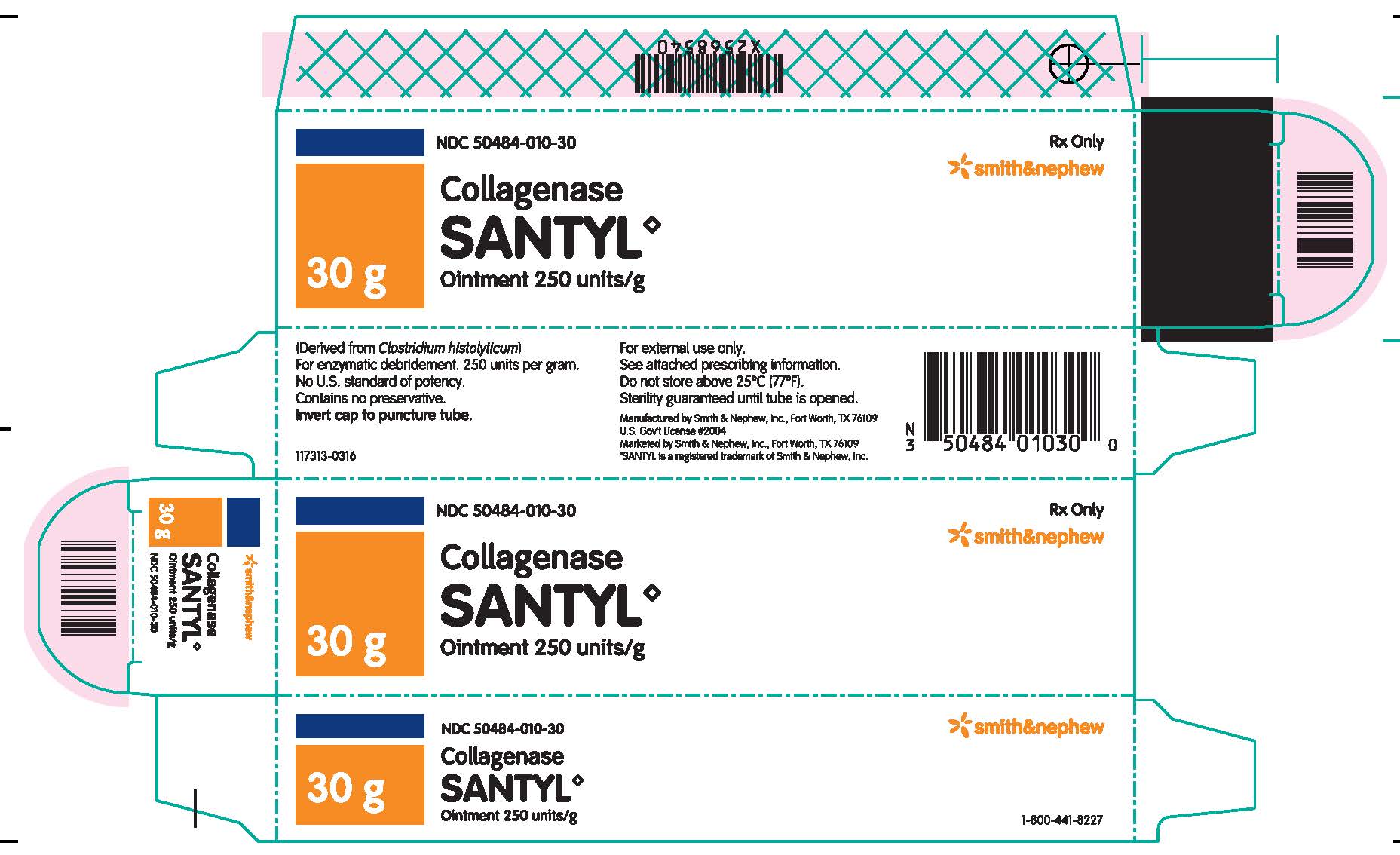 DRUG LABEL: COLLAGENASE SANTYL
NDC: 50484-010 | Form: OINTMENT
Manufacturer: SMITH & NEPHEW, INC
Category: prescription | Type: HUMAN PRESCRIPTION DRUG LABEL
Date: 20190517

ACTIVE INGREDIENTS: COLLAGENASE CLOSTRIDIUM HISTOLYTICUM 250 [arb'U]/1 g
INACTIVE INGREDIENTS: PETROLATUM

COLLAGENASE SANTYL◊ ointment
250 units/g
[SMITH & NEPHEW, INC]

Rx only

DESCRIPTION

Collagenase Santyl◊ Ointment is a sterile enzymatic debriding ointment which contains 250 collagenase units per gram of white petrolatum USP. The enzyme collagenase is derived from the fermentation by Clostridium histolyticum. It possesses the unique ability to digest collagen in necrotic tissue.

CLINICAL PHARMACOLOGY

Since collagen accounts for 75% of the dry weight of skin tissue, the ability of collagenase to digest collagen in the physiological pH and temperature range makes it particularly effective in the removal of detritus.^1 Collagenase thus contributes towards the formation of granulation tissue and subsequent epithelization of dermal ulcers and severely burned areas.^(2, 3, 4, 5, 6) Collagen in healthy tissue or in newly formed granulation tissue is not attacked.^(2, 3, 4, 5, 6, 7, 8) There is no information available on collagenase absorption through skin or its concentration in body fluids associated with therapeutic and/or toxic effects, degree of binding to plasma proteins, degree of uptake by a particular organ or in the fetus, and passage across the blood brain barrier.

INDICATIONS AND USAGE

Collagenase Santyl◊ Ointment is indicated for debriding chronic dermal ulcers ^(2, 3, 4, 5, 6, 8, 9, 10, 11, 12, 13, 14, 15, 16, 17, 18) and severely burned areas. ^(3, 4, 5, 7, 16, 19, 20, 21)

CONTRAINDICATIONS

Collagenase Santyl◊ Ointment is contraindicated in patients who have shown local or systemic hypersensitivity to collagenase.

PRECAUTIONS

The optimal pH range of collagenase is 6 to 8. Higher or lower pH conditions will decrease the enzyme’s activity and appropriate precautions should be taken. The enzymatic activity is also adversely affected by certain detergents, and heavy metal ions such as mercury and silver which are used in some antiseptics. When it is suspected such materials have been used, the site should be carefully cleansed by repeated washings with normal saline before Collagenase Santyl◊ Ointment is applied. Soaks containing metal ions or acidic solutions should be avoided because of the metal ion and low pH. Cleansing materials such as Dakin’s solution and normal saline are compatible with Collagenase Santyl◊ Ointment.

Debilitated patients should be closely monitored for systemic bacterial infections because of the theoretical possibility that debriding enzymes may increase the risk of bacteremia.

A slight transient erythema has been noted occasionally in the surrounding tissue, particularly when Collagenase Santyl◊ Ointment was not confined to the wound. Therefore, the ointment should be applied carefully within the area of the wound. Safety and effectiveness in pediatric patients have not been established.

ADVERSE REACTIONS

No allergic sensitivity or toxic reactions have been noted in clinical use when used as directed. However, one case of systemic manifestations of hypersensitivity to collagenase in a patient treated for more than one year with a combination of collagenase and cortisone has been reported.

OVERDOSAGE

No systemic or local reaction attributed to overdose has been observed in clinical investigations and clinical use. If deemed necessary the enzyme may be inactivated by washing the area with povidone iodine.

DOSAGE AND ADMINISTRATION

Collagenase Santyl◊ Ointment should be applied once daily (or more frequently if the dressing becomes soiled, as from incontinence). When clinically indicated, crosshatching thick eschar with a #10 blade allows Collagenase Santyl◊ Ointment more surface contact with necrotic debris. It is also desirable to remove, with forceps and scissors, as much loosened detritus as can be done readily. Use Collagenase Santyl◊ Ointment in the following manner:

1 - Prior to application the wound should be cleansed of debris and digested material by gently rubbing with a gauze pad saturated with normal saline solution, or with the desired cleansing agent compatible with Collagenase Santyl◊ Ointment (See PRECAUTIONS), followed by a normal saline solution rinse.

2 - Whenever infection is present, it is desirable to use an appropriate topical antibiotic powder. The antibiotic should be applied to the wound prior to the application of Collagenase Santyl◊ Ointment. Should the infection not respond, therapy with Collagenase Santyl◊ Ointment should be discontinued until remission of the infection.

3 - Collagenase Santyl◊ Ointment may be applied directly to the wound or to a sterile gauze pad which is then applied to the wound and properly secured.

4 - Use of Collagenase Santyl◊ Ointment should be terminated when debridement of necrotic tissue is complete and granulation tissue is well established.

HOW SUPPLIED

Collagenase Santyl◊ Ointment contains 250 units of collagenase enzyme per gram of white petrolatum USP.

Do not store above 25°C (77°F). Sterility guaranteed until tube is opened.

Collagenase Santyl◊ Ointment is available in the following sizes:

30 g tube NDC 50484-010-30

90 g tube NDC 50484-010-90

REFERENCES

1 – Mandl, I., Adv Enzymol. 23:163, 1961.

2 – Boxer, A.M., Gottesman, N., Bernstein, H., &amp; Mandl, I., Geriatrics. 24:75, 1969.

3 – Mazurek, I., Med. Welt. 22:150, 1971.

4 – Zimmermann, WE., in “Collagenase,” Mandl, I., ed., Gordon &amp; Breach, Science Publishers, New York, 1971, p. 131, p. 185.

5 – Vetra, H., &amp; Whittaker, D., Geriatrics. 30:53, 1975.

6 – Rao, D.B., Sane, P.G., &amp; Georgiev, E.L., J. Am. Geriatrics Soc. 23:22, 1975.

7 – Vrabec, R., Moserova, J., Konickova, Z., Behounkova, E., &amp; Blaha, J., J. Hyg. Epidemiol. Microbiol. Immunol. 18:496, 1974.

8 – Lippmann, H.I., Arch. Phys. Med. Rehabil. 54:588, 1973.

9 – German, F. M., in “Collagenase,” Mandl, I., ed., Gordon &amp; Breach, Science Publishers, New York, 1971, p. 165.

10 – Haimovici, H. &amp; Strauch, B., in “Collagenase,” Mandl, I., ed., Gordon &amp; Breach, Science Publishers, New York, 1971, p. 177.

11 – Lee, L.K., &amp; Ambrus, J.L., Geriatrics. 30:91, 1975.

12 – Locke, R.K., &amp; Heifitz, N.M., J. Am. Pod. Assoc. 65:242, 1975.

13 – Varma, A.O., Bugatch, E., &amp; German, F.M., Surg. Gynecol. Obstet. 136:281, 1973.

14 – Barrett, D., Jr., &amp; Klibanski, A., Am. J. Nurs. 73:849, 1973.

15 – Bardfeld, L.A., J. Pod. Ed. 1:41, 1970.

16 – Blum, G., Schweiz, Rundschau Med Praxis. 62:820, 1973. Abstr. in Dermatology Digest, Feb. 1974, p. 36.

17 – Zaruba, F., Lettl, A., Brozkova, L., Skrdlantova, H., &amp; Krs, V., J. Hyg. Epidemiol. Microbiol. Immunol. 18:499, 1974.

18 – Altman, M.I., Goldstein, L., &amp; Horwitz, S., J. Am. Pod. Assoc. 68:11, 1978.

19 – Rehn, V.J., Med. Klin. 58:799, 1963.

20 – Krauss, H., Koslowski, L., &amp; Zimmermann, W. E., Langenbecks Arch. Klin. Chir. 303:23, 1963.

21 – Gruenagel, H.H., Med. Klin. 58:442, 1963.

Manufactured by:
SMITH & NEPHEW, INC
Fort Worth, Texas 76109

US Gov’t License #2004

Marketed by:
Smith & Nephew◊

1-800-441-8227

Smith & Nephew, Inc.,
Fort Worth, Texas 76109

© 2016 Smith & Nephew, Inc.

SANTYL is a registered trademark of Smith & Nephew, Inc.

140749-0316